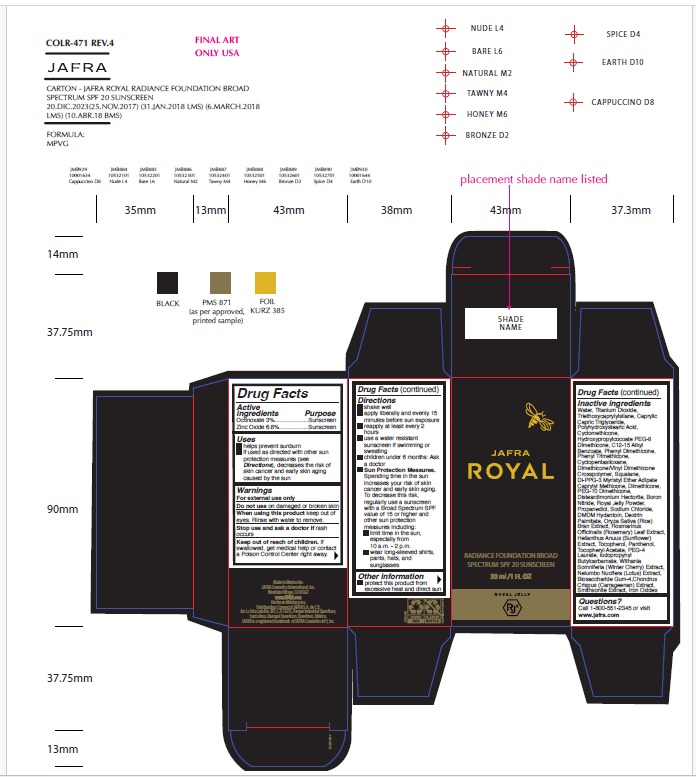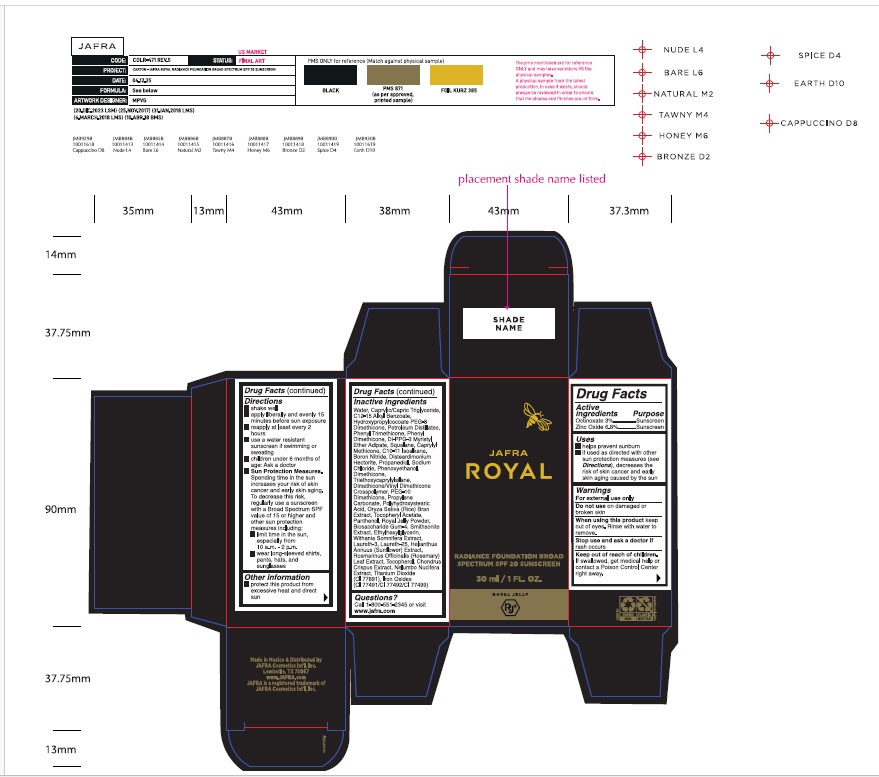 DRUG LABEL: Radiance Foundation Broad Spectrum SPF 20-Nude
NDC: 68828-732 | Form: LIQUID
Manufacturer: Distribuidora Comercial Jafra, S.A. de C.V.
Category: otc | Type: HUMAN OTC DRUG LABEL
Date: 20251231

ACTIVE INGREDIENTS: OCTINOXATE 3 g/100 mL; ZINC OXIDE 6.8 g/100 mL
INACTIVE INGREDIENTS: WATER; TITANIUM DIOXIDE; TRIETHOXYCAPRYLYLSILANE; MEDIUM-CHAIN TRIGLYCERIDES; POLYHYDROXYSTEARIC ACID (2300 MW); HYDROXYPROPYLCOCOATE PEG-8 DIMETHICONE; ALKYL (C12-15) BENZOATE; PHENYL TRIMETHICONE; DIMETHICONE/VINYL DIMETHICONE CROSSPOLYMER (SOFT PARTICLE); SQUALANE; DI-PPG-3 MYRISTYL ETHER ADIPATE; CAPRYLYL TRISILOXANE; DIMETHICONE, UNSPECIFIED; PEG-10 DIMETHICONE (600 CST); DISTEARDIMONIUM HECTORITE; BORON NITRIDE; ROYAL JELLY; PROPANEDIOL; SODIUM CHLORIDE; RICE BRAN; ROSEMARY; HELIANTHUS ANNUUS FLOWERING TOP; TOCOPHEROL; PANTHENOL; .ALPHA.-TOCOPHEROL ACETATE; WITHANIA SOMNIFERA FLOWER; BIOSACCHARIDE GUM-4; CHONDRUS CRISPUS CARRAGEENAN; FERRIC OXIDE RED; FERRIC OXIDE YELLOW; FERROSOFERRIC OXIDE; NELUMBO NUCIFERA FLOWER; C10-11 ISOPARAFFIN; PHENOXYETHANOL; PROPYLENE CARBONATE; ETHYLHEXYLGLYCERIN; LAURETH-3; LAURETH-25

Radiance Foundation Broad Spectrum SPF 20-Nude

Active ingredients

Octinoxate 3%

Zinc Oxide 6.8%

Purpose

Sunscreen

Uses

- helps prevent sunburn
- if used as directed with other sun protection measures (see Directions), decreases the risk of skin cancer and early skin aging caused by the sun

Warnings

For external use only

Do not use on damaged or broken skin

When using this product keep out of eyes. Rinse with water to remove.

Stop use and ask a doctor if rash occurs

Keep out of reach of children. If swallowed, get medical help or contact a Poison Control Center right away.

Directions

• shake well
• apply liberally and evenly 15 minutes before sun exposure
• reapply at least every 2 hours
• use a water resistant sunscreen if swimming or sweating
• children under 6 months of age: Ask a doctor
• Sun Protection Measures. Spending time in the sun increases your risk of skin cancer and early skin aging. To decrease this risk, regularly use a sunscreen with a Broad Spectrum SPF value of 15 or higher and other sun protection measures including:
o limit time in the sun, especially from 10 a.m.-2 p.m.
o wear long-sleeved shirts, pants, hats, and sunglasses

Other information

- protect this product from excessive heat and direct sun

Inactive Ingredients.

Water, Caprylic/Capric Triglyceride, C12-15 Alkyl Benzoate, Hydroxypropylcocoate PEG-8 Dimethicone, Petroleum Distillates, Phenyl Trimethicone, Phenyl Dimethicone, Di-PPG-3 Myristyl Ether Adipate, Squalane, Caprylyl Methicone, C10-11 Isoalkane, Boron Nitride, Disteardimonium Hectorite, Propanediol, Sodium Chloride, Phenoxyethanol, Dimethicone, Triethoxycaprylylsilane, Dimethicone/Vinyl Dimethicone Crosspolymer, PEG-10 Dimethicone, Propylene Carbonate, Polyhydroxystearic Acid, Oryza Sativa (Rice) Bran Extract, Tocopheryl Acetate, Panthenol, Royal Jelly Powder, Biosaccharide Gum-4, Smithsonite Extract, Ethylhexylglycerin, Withania Somnifera Extract, Laureth-3, Laureth-25, Helianthus Annuus (Sunflower) Extract, Rosmarinus Officinalis (Rosemary) Leaf Extract, Tocopherol, Chondrus Crispus Extract, Nelumbo Nucifera Extract, Titanium Dioxide (CI 77891), Iron Oxides (CI 77491/CI 77492/CI 77499)

Questions?

Call 1-800-551-2345 or visit www.jafra.com